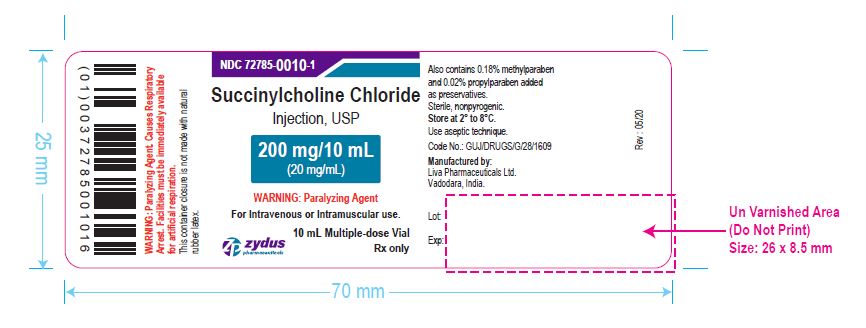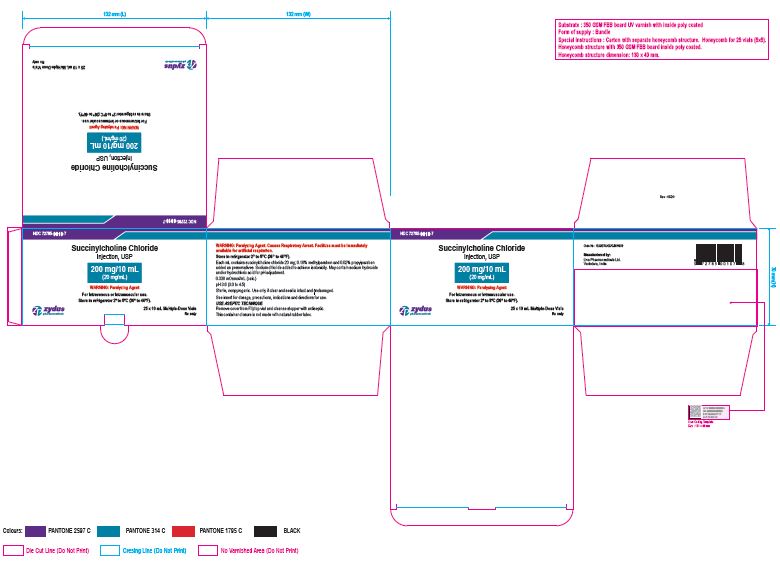 DRUG LABEL: Succinylcholine Chloride
NDC: 72785-0010 | Form: INJECTION, SOLUTION
Manufacturer: Liva Pharmaceuticals Limited
Category: prescription | Type: HUMAN PRESCRIPTION DRUG LABEL
Date: 20200514

ACTIVE INGREDIENTS: SUCCINYLCHOLINE CHLORIDE 20 mg/1 mL
INACTIVE INGREDIENTS: HYDROCHLORIC ACID; METHYLPARABEN 1.8 mg/1 mL; PROPYLPARABEN 0.2 mg/1 mL; SODIUM CHLORIDE; SODIUM HYDROXIDE

Succinylcholine Chloride Injection, USP
A short-acting depolarizing skeletal muscle relaxant.

PACKAGE LABEL.PRINCIPAL DISPLAY PANEL

Vial Label

NDC 72785-0010-1

Succinylcholine Chloride Injection, USP

200 mg/10 mL (20 mg/mL)

For Intravenous or Intramuscular use.

10 mL Multiple-dose Vial

Rx only

Carton Label

NDC 72785-0010-7

Succinylcholine Chloride Injection, USP

200 mg/10 mL (20 mg/mL)

For Intravenous or Intramuscular use.

Store in refrigerator 2º to 8ºC (36º to 46ºF).

25 x 10 mL Multiple-dose Vial

Rx only